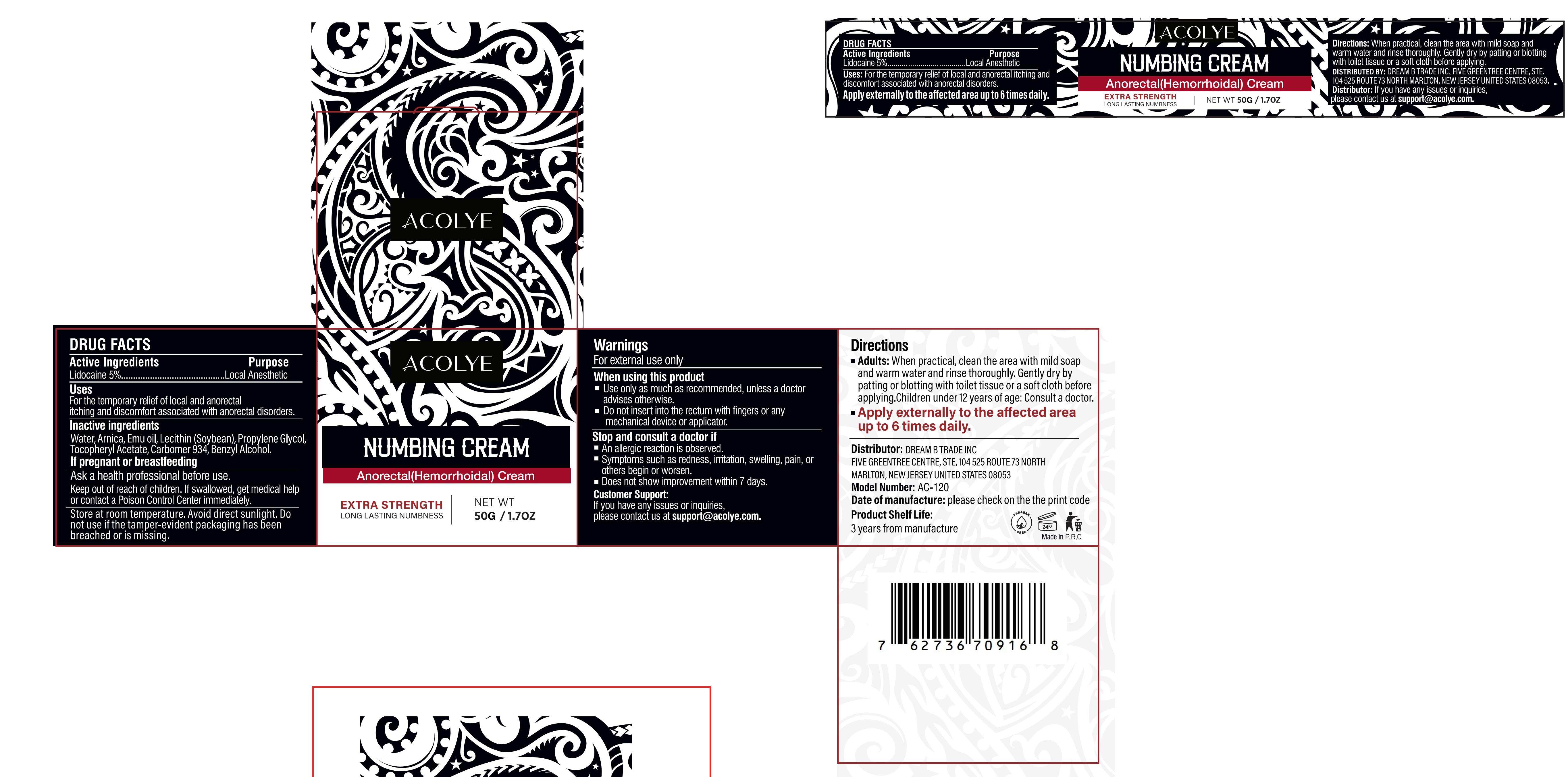 DRUG LABEL: Acolye Numbing Cream  Anorectal(Hemorrhoidal) Cream
NDC: 60771-0028 | Form: CREAM
Manufacturer: Guangzhou Haishi Biological Technology Co., Ltd.
Category: otc | Type: HUMAN OTC DRUG LABEL
Date: 20251009

ACTIVE INGREDIENTS: LIDOCAINE 5 g/100 g
INACTIVE INGREDIENTS: ARNICA MONTANA FLOWER; EMU OIL; BENZYL ALCOHOL; WATER; .ALPHA.-TOCOPHEROL ACETATE; CARBOMER 934; PROPYLENE GLYCOL; LECITHIN, SOYBEAN

Acolye Numbing Cream Anorectal(Hemorrhoidal) Cream

Active Ingredients

LIDOCAINE 5%

Purpose

For the temporary relief of local and anorectal itching and discomfort associated with anorectal disorders

Uses

Directions
Adults: When practical, clean the area with mild soap and warm water and rinse thoroughly. Gently dry by patting or blotting with toilet tissue or a soft cloth before applying.Children under 12 years of age: Consult a doctor.
Apply externally to the affected area up to 6 times daily.

Warnings

For external use only

Stop Use

Stop and consult a doctor if
An allergic reaction is observed.
Symptoms such as redness, irritation, swelling, pain, or others begin or worsen.
Does not show improvement within 7 days.

Do Not Use

on damaged or broken skin.

When Using

When using this product
Use only as much as recommended, unless a doctor advises otherwise.

Do not insert into the rectum with fingers or any mechanical device or applicator.

Keep Out Of Reach Of Children

If swallowed, get medical help or contact a Poison Control Center immediately.

Inactive ingredients

Water: 82%
Arnica: 2%
Emu oil: 2%
Lecithin (Soybean): 2%
Propylene Glycol: 2%
Tocopheryl Acetate: 2%
Carbomer 934: 2%
Benzyl Alcohol: 1%

Dosage & administration

Squeeze out an appropriate amount of Numbing Cream and spread evenly on skin.